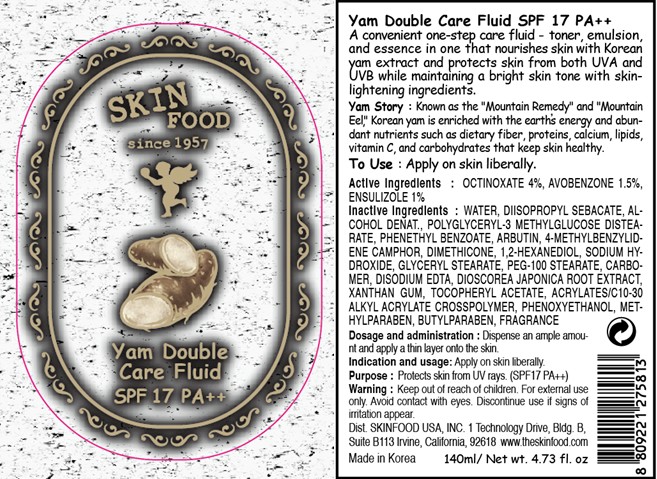 DRUG LABEL: YAM DOUBLE CARE FLUID
NDC: 76214-015 | Form: CREAM
Manufacturer: SKINFOOD CO., LTD.
Category: otc | Type: HUMAN OTC DRUG LABEL
Date: 20110907

ACTIVE INGREDIENTS: OCTINOXATE 5.6 mL/140 mL; AVOBENZONE 2.1 mL/140 mL; ENSULIZOLE 1.4 mL/140 mL
INACTIVE INGREDIENTS: WATER; DIISOPROPYL SEBACATE; PHENETHYL BENZOATE; ARBUTIN; ENZACAMENE; DIMETHICONE; PHENOXYETHANOL; 1,2-HEXANEDIOL; SODIUM HYDROXIDE; GLYCERYL MONOSTEARATE; PEG-100 STEARATE; METHYLPARABEN; BUTYLPARABEN; EDETATE DISODIUM; DIOSCOREA JAPONICA ROOT; XANTHAN GUM

Drug Facts

ACTIVE INGREDIENT

Active ingredients: OCTINOXATE 4.0%, AVOBENZONE 1.5%, ENSULIZOLE 1.0%

Inactive ingredients:
WATER, DIISOPROPYL SEBACATE, ALCOHOL DENAT., POLYGLYCERYL-3 METHYLGLUCOSE DISTEARATE, PHENETHYL BENZOATE, ARBUTIN, 4-METHYLBENZYLIDENE CAMPHOR, DIMETHICONE, 1,2-HEXANEDIOL, SODIUM HYDROXIDE, GLYCERYL STEARATE, PEG-100 STEARATE, CARBOMER, DISODIUM EDTA, DIOSCOREA JAPONICA ROOT EXTRACT, XANTHAN GUM,
TOCOPHERYL ACETATE, ACRYLATES/C10-30 ALKYL ACRYLATE CROSSPOLYMER, PHENOXYETHANOL, METHYLPARABEN, BUTYLPARABEN, FRAGRANCE

Purpose: Protects skin from UV rays.

Warnings:
For external use only. Avoid contact with eyes.
Discontinue use if signs of irritation appear.

Keep out of reach of children:
Keep out of reach of children.

Indication and usage: Apply on skin liberally.

Dosage and administration: Dispense an ample amount and apply a thin layer onto the skin.